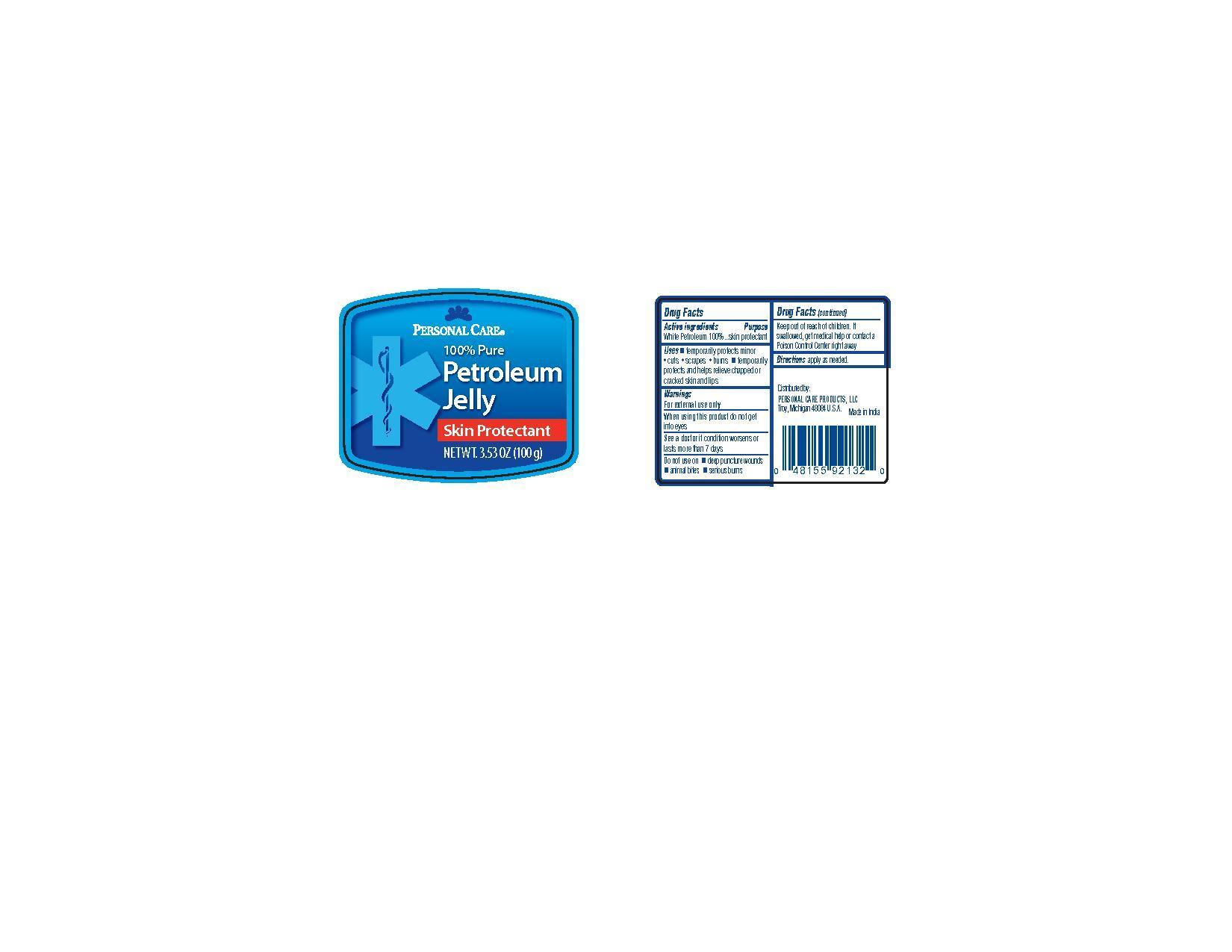 DRUG LABEL: Personal Care Petroleum
                
                
NDC: 29500-8020 | Form: JELLY
Manufacturer: Personal Care Products
Category: otc | Type: HUMAN OTC DRUG LABEL
Date: 20120626

ACTIVE INGREDIENTS: PETROLATUM 100 g/100 g

Personal Care 100% Petroleum

Active Ingredients

White Petroleum 100%

Purpose skin protectant

Keep out of reach of children. If swallowed ge medical help or contact a Poison Control Center right away.

Uses

Temporarily protects minor cuts, scrapes, burns

Temporarily protects and helps relieve chapped or cracked skin and lips

Warnings

For external use only

When using this product do not get into eyes

See a doctor if condition worsens or lasts more than 7 days

Do not use on deep puncture wounds, animal bites, serious burns

DOSAGE AND ADMINISTRATION

Directions apply as needed

Inactive ingredients None

PACKAGE LABEL

Personal Care

100% petroleum Jelly

Skin protectant

Net wt 3.53 oz (100 g)

Distributed by

Personal Care Products, LLC

Troy Michigan 48084

Made in india